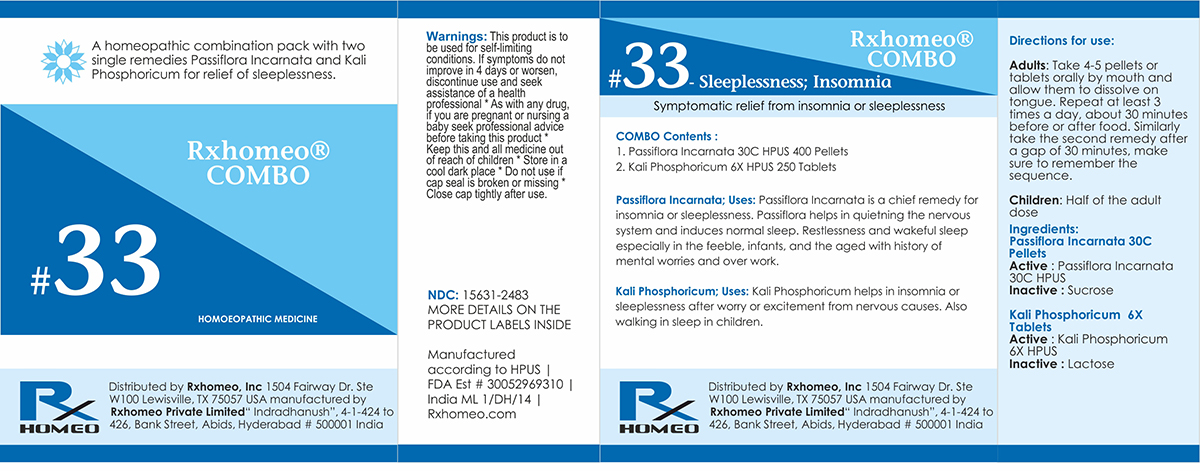 DRUG LABEL: Rxhomeo Homeopathic Combo
NDC: 15631-2483 | Form: KIT | Route: ORAL
Manufacturer: Rxhomeo Private Limited d.b.a.
Category: homeopathic | Type: HUMAN OTC DRUG LABEL
Date: 20161013

ACTIVE INGREDIENTS: PASSIFLORA INCARNATA FLOWERING TOP 1 [hp_X]/1 1; POTASSIUM PHOSPHATE, DIBASIC 1 [hp_X]/1 1
INACTIVE INGREDIENTS: SUCROSE; LACTOSE

ACTIVE INGREDIENT

PASSIFLORA INCARNATA HPUS 3X and higher

KALI PHOSPHORICUM HPUS 1X and Higher

USES

A homeopathic combination pack with two single remedies Passiflora Incarnata and Kali Phosphoricum for relief of sleeplessness.

Passiflora Incarnata; Uses: Passiflora Incarnata is a chief remedy for insomnia or sleeplessness. Passiflora helps in quietning the nervous system and induces normal sleep. Restlessness and wakeful sleep especially in the feeble, infants, and the aged with history of mental worries and over work.

Kali Phosphoricum;Uses: Kali Phosphoricum helps in insomnia or sleeplessness after worry or excitement from nervous causes. Also walking in sleep in children.

INDICATIONS

Condition listed above or as directed by the physician

DOSAGE

PELLETS included in the Combo

Adults- Take 4 or 6 Pellets by mouth, three times daily or as suggested by physician. Children 2 years and older- take 1/2 the adult dose.

TABLETS included in the Combo

Adults- Take 4 or 6 Tablets by mouth, three times daily or as suggested by physician. Children 2 years and older- take 1/2 the adult dose.

WARNINGS

This product is to be used for self-limiting conditions

STOP USE

If symptoms do not improve in 4 days, or worsen, discontinue use and seek assistance of health professional

KEEP OUT OF REACH OF CHILDREN

Keep this and all medication out of reach of children

Do not use if capseal is broken or missing.

Close the cap tightly after use.

INACTIVE INGREDIENTS

Sucrose for Pellets.

Lactose for Tablets.

STORAGE

Store in a cool dark place

QUESTIONS OR COMMENTS

www.Rxhomeo.com | 1.888.2796642 | info@rxhomeo.com
Rxhomeo, Inc 1504 Fairway Dr. Ste W 100 Lewisville, TX 75057 USA